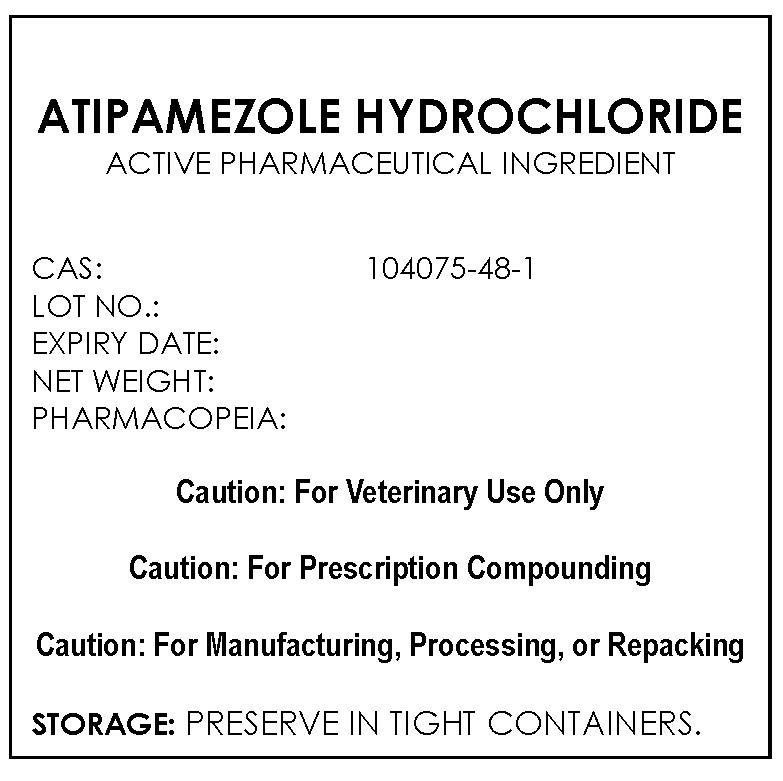 DRUG LABEL: ATIPAMEZOLE HYDROCHLORIDE
NDC: 43744-021 | Form: POWDER
Manufacturer: CBSCHEM LIMITED
Category: other | Type: BULK INGREDIENT
Date: 20210202

ACTIVE INGREDIENTS: ATIPAMEZOLE HYDROCHLORIDE 1 g/1 g

ATIPAMEZOLE HYDROCHLORIDE

PACKAGE LABEL

atipamezolehydrochloridelabelfile.jpg